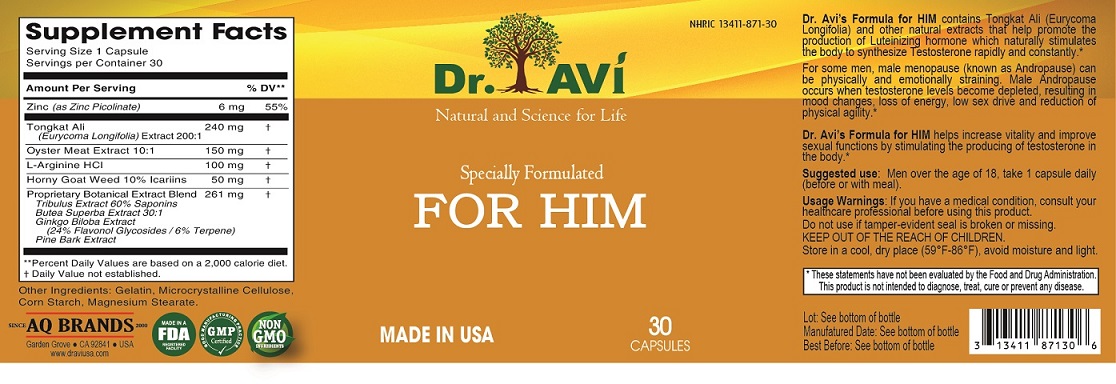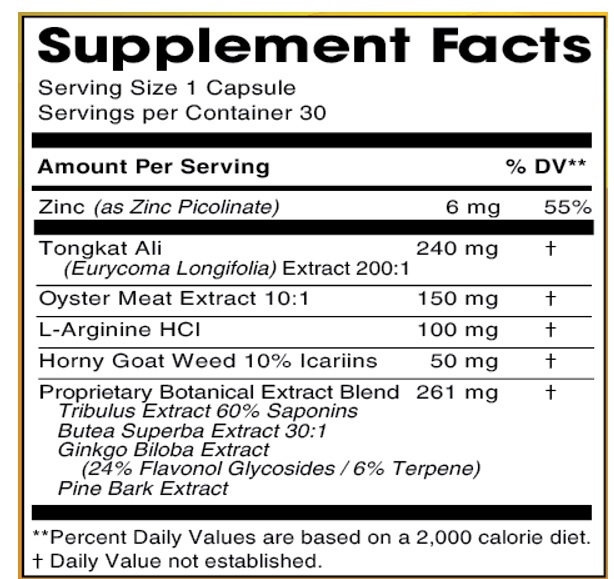 DRUG LABEL: Dr. Avi for Him
NDC: 13411-871 | Form: CAPSULE
Manufacturer: Advanced Pharmaceutical Services, Inc. Dba Affordable Quality Pharmaceuticals
Category: other | Type: DIETARY SUPPLEMENT
Date: 20210406

ACTIVE INGREDIENTS: ZINC PICOLINATE 6 mg/1 1; EURYCOMA LONGIFOLIA ROOT 240 mg/1 1; ARGININE HYDROCHLORIDE 100 mg/1 1; EPIMEDIUM GRANDIFLORUM TOP 50 mg/1 1; TRIBULUS TERRESTRIS FRUIT 100 mg/1 1; GINKGO 40 mg/1 1; MARITIME PINE 40 mg/1 1; BUTEA SUPERBA ROOT 81 mg/1 1; EDIBLE OYSTER 150 mg/1 1
INACTIVE INGREDIENTS: GELATIN, UNSPECIFIED; MICROCRYSTALLINE CELLULOSE; STARCH, CORN; MAGNESIUM STEARATE

Identity

DIETARY SUPPLEMENT

Warning

If you have a medical condition, consult your healthcare professional before using this product.

Safe handling and warning

Do not use if tamper-evident seal is broken or missing.

Store in a cool, dry place (59°F-86°F), avoid moisture and light.

Health claim

Dr. Avi’s Formula for HIM contains Tongkat Ali (Eurycoma Longifolia) and other natural extracts that help promote the production of Luteinizing hormone which naturally stimulates the body to synthesize Testosterone rapidly and constantly.*
For some men, male menopause (known as Andropause) can be physically and emotionally straining. Male Andropause occurs when testosterone levels become depleted, resulting in mood changes, loss of energy, low sex drive and reduction of physical agility.*
Dr. Avi’s Formula for HIM helps increase vitality and improve sexual functions by stimulating the producing of testosterone in the body.*

* These statements have not been evaluated by the Food & Drug Administration. This product is not intended to diagnose, treat, cure, or prevent any disease.

Direction

Men over the age of 18, take 1 capsule daily (before or with meal).